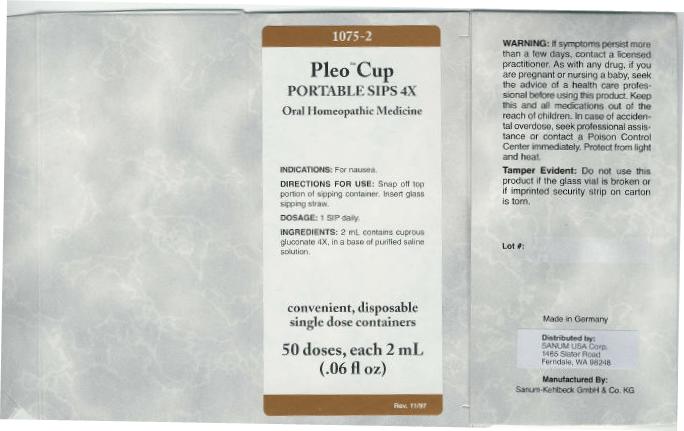 DRUG LABEL: Pleo Cup
NDC: 60681-1075 | Form: LIQUID
Manufacturer: Sanum Kehlbeck GmbH & Co. KG
Category: homeopathic | Type: HUMAN OTC DRUG LABEL
Date: 20091130

ACTIVE INGREDIENTS: copper gluconate 4 [hp_X]/2 mL
INACTIVE INGREDIENTS: sodium chloride; water

Pleo™ Cup
PORTABLE SIPS 4X

Oral Homeopathic Medicine

INDICATIONS

For nausea.

DIRECTIONS FOR USE

Snap off top portion of sipping container. Insert glass sipping straw.

DOSAGE

1 SIP daily.

INGREDIENTS

2 mL contains cuprous gluconate 4X, in a base of purified saline solution.

WARNING

If symptoms persist more than a few days, contact a licensed practitioner. As with any drug, if you are pregnant or nursing a baby, seek the advice of a health care professional before using this product.

KEEP OUT OF REACH OF CHILDREN

Keep this and all medications out of the reach of children. In case of accidental overdose , seek professional assistance or contact a Poison Control Center immediately.

STORAGE AND HANDLING

Protect from light and heat.

Tamper Evident

Do not use this product if the glass vial is broken or if imprinted security strip on carton is torn.

Made in Germany

Distributed by:
SANUM USA Corp.
1465 Slater Road
Ferndale, WA 98248

Manufactured By:
Sanum-Kehlbeck GmbH & Co. KG

PRINCIPAL DISPLAY PANEL - 2 mL Carton

1075-2

Pleo™ Cup
PORTABLE SIPS 4X

Oral Homeopathic Medicine

INDICATIONS: For nausea.

DIRECTIONS FOR USE: Snap off top
portion of sipping container. Insert glass
sipping straw.

DOSAGE: 1 SIP daily.

INGREDIENTS: 2 mL contains cuprous
gluconate 4X, in a base of purified saline
solution.

convenient, disposable
single dose containers

50 doses, each 2 mL
(0.6 fl oz)

Rev. 11/97